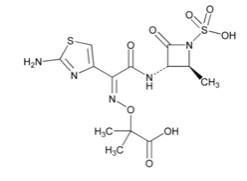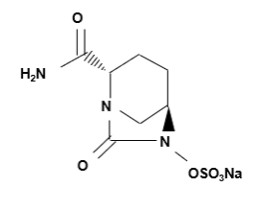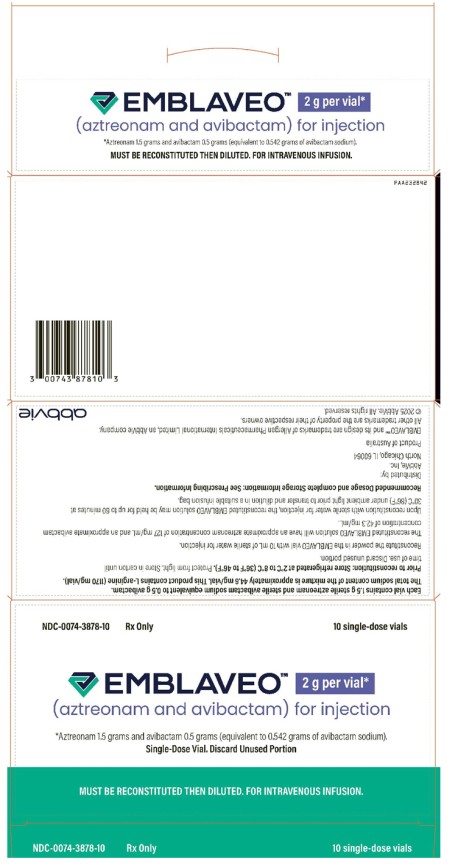 DRUG LABEL: EMBLAVEO
NDC: 0074-3878 | Form: POWDER, FOR SOLUTION
Manufacturer: AbbVie Inc.
Category: prescription | Type: HUMAN PRESCRIPTION DRUG LABEL
Date: 20250207

ACTIVE INGREDIENTS: AZTREONAM 127 mg/1 mL; AVIBACTAM 42.3 mg/1 mL
INACTIVE INGREDIENTS: ARGININE 99.1 mg/1 mL

HIGHLIGHTS OF PRESCRIBING INFORMATION

These highlights do not include all the information needed to use EMBLAVEO safely and effectively. See full prescribing information for EMBLAVEO.
EMBLAVEO (aztreonam and avibactam) for injection, for intravenous use
Initial U.S. Approval: 2025

1 INDICATIONS AND USAGE

EMBLAVEO is a combination of aztreonam, a monobactam antibacterial, and avibactam, a beta-lactamase inhibitor, that when used in combination with metronidazole, is indicated in patients 18 years and older who have limited or no alternative options for the treatment of complicated intra-abdominal infections (cIAI) including those caused by the following susceptible gram-negative microorganisms: Escherichia coli, Klebsiella pneumoniae, Klebsiella oxytoca, Enterobacter cloacae complex, Citrobacter freundii complex, and Serratia marcescens. Approval of this indication is based on limited clinical safety and efficacy data for EMBLAVEO. (1.1)

Usage to Reduce Development of Drug-Resistant Bacteria

To reduce the development of drug-resistant bacteria and maintain the effectiveness of EMBLAVEO and other antibacterial drugs, EMBLAVEO should be used only to treat infections that are proven or strongly suspected to be caused by bacteria. (1.2)

2 DOSAGE AND ADMINISTRATION

Recommended Dosage in Adults based on Estimated Creatinine Clearance (CLcr) (2.1, 2.2)
Estimated CLcr (mL/min) a | Doseb |  | Infusion Time | Dosing Intervalc
 | Loading | Maintenance
Greater than 50 mL/min | EMBLAVEO 2.67 g (aztreonam 2 grams and avibactam 0.67 grams) | EMBLAVEO 2 g (aztreonam 1.5 grams and avibactam 0.5 grams) | 3 hours | Every 6 hours
Greater than 30 to less than or equal to 50 mL/min | EMBLAVEO 2.67 g (aztreonam 2 grams and avibactam 0.67 grams) | EMBLAVEO 1 g (aztreonam 0.75 grams and avibactam 0.25 grams) | 3 hours | Every 6 hours
Greater than 15 to less than or equal to 30 mL/min | EMBLAVEO 1.8 g (aztreonam 1.35 grams and avibactam 0.45 grams) | EMBLAVEO 0.9 g (aztreonam 0.675 grams and avibactam 0.225 grams) | 3 hours | Every 8 hours
Less than or equal to 15 mL/min, including on hemodialysisd | EMBLAVEO 1.33 g (aztreonam 1 gram and avibactam 0.33 grams) | EMBLAVEO 0.9 g (aztreonam 0.675 grams and avibactam 0.225 grams) | 3 hours | Every 12 hours
aCalculated using the Cockcroft-Gault formula.
bAztreonam-avibactam is a combination product in a fixed 3:1 ratio. A single loading dose is followed by maintenance doses beginning at the next dosing interval.
cDosing interval is calculated from the start of one infusion to the start of the subsequent infusion.
dBoth aztreonam and avibactam are removed by hemodialysis; thus, administer EMBLAVEO after hemodialysis, on hemodialysis days.

- For treatment of cIAI, administer metronidazole concurrently. (2.1, 2.2)
- Recommended duration of treatment for cIAI: 5 to 14 days. (2.1, 2.2)

3 DOSAGE FORMS AND STRENGTHS

- EMBLAVEO (aztreonam and avibactam) for injection is a lyophilized powder in a single-dose vial containing 2 g (1.5 grams aztreonam and 0.5 grams avibactam). (3)

4 CONTRAINDICATIONS

- Known hypersensitivity to the components of EMBLAVEO (aztreonam and avibactam). (4)

5 WARNINGS AND PRECAUTIONS

- Hypersensitivity Reactions: Hypersensitivity reactions were noted in patients treated with EMBLAVEO including rash, flushing, and bronchospasm. In case of hypersensitivity reactions, immediately discontinue EMBLAVEO and initiate appropriate medications and/or supportive care. (5.1)
- Serious Skin Disorders: Cases of toxic epidermal necrolysis have been reported in association with aztreonam (a component of EMBLAVEO) in patients undergoing bone marrow transplant with multiple risk factors. Discontinue EMBLAVEO if serious skin reaction occurs. (5.2)
- Hepatic Adverse Reactions: Elevations in hepatic transaminases have been observed during treatment with EMBLAVEO. If transaminase elevations are noted, consider discontinuation of EMBLAVEO, if clinically indicated, and monitor the patient for resolution of any pertinent clinical and laboratory findings. (5.3)
- Clostridioides Difficile-Associated Diarrhea (CDAD): CDAD has been reported with nearly all systemic antibacterial agents, including EMBLAVEO. Evaluate if diarrhea occurs. (5.4)

6 ADVERSE REACTIONS

The most common adverse reactions occurring at an incidence of greater than 5% were hepatic adverse reactions, anemia, diarrhea, hypokalemia, and pyrexia. (6.1)

To report SUSPECTED ADVERSE REACTIONS, contact AbbVie Inc. at 1-800-633-9110 or FDA at 1-800-FDA-1088 or www.fda.gov/medwatch

FULL PRESCRIBING INFORMATION

1 INDICATIONS AND USAGE

1.1 Complicated Intra-abdominal Infections

EMBLAVEO, in combination with metronidazole, is indicated in patients 18 years and older who have limited or no alternative options for the treatment of complicated intra-abdominal infections (cIAI) including those caused by the following susceptible gram-negative microorganisms: Escherichia coli, Klebsiella pneumoniae, Klebsiella oxytoca, Enterobacter cloacae complex, Citrobacter freundii complex, and Serratia marcescens. Approval of this indication is based on limited clinical safety and efficacy data for EMBLAVEO [see Clinical Studies (14.1)].

1.2 Usage to Reduce Development of Drug-Resistant Bacteria

To reduce the development of drug-resistant bacteria and maintain the effectiveness of EMBLAVEO and other antibacterial drugs, EMBLAVEO should be used only to treat infections that are proven or strongly suspected to be caused by susceptible bacteria. When culture and susceptibility information are available, they should be considered in selecting or modifying antibacterial therapy. In the absence of such data, local epidemiology and susceptibility patterns may contribute to the empiric selection of therapy.

2 DOSAGE AND ADMINISTRATION

2.1 Recommended Dosage in Adults with Estimated Creatinine Clearance Greater than 50 mL/min

Table 1 shows the recommended dosage to be administered by intravenous (IV) infusion over 3 hours in adults with estimated creatinine clearance (CLcr) greater than 50 mL/min.

Table 1. Recommended dosage for adults with estimated CLcr greater than 50 mL/mina
Type of Infection | Recommended Doses for EMBLAVEO (aztreonam and avibactam) b |  | Dosing Intervalc | Treatment duration
Complicated intra-abdominal infections (cIAI)d | Loading | EMBLAVEO 2.67 g (aztreonam 2 grams and avibactam 0.67 grams) | Every 6 hours | 5 to 14 days
 | Maintenance | EMBLAVEO 2 g (aztreonam 1.5 grams and avibactam 0.5 grams)
aCalculated using the Cockcroft-Gault formula.
bAztreonam-avibactam is a combination product in a fixed 3:1 ratio. A single loading dose is followed by maintenance doses beginning at the next dosing interval.
cDosing interval is calculated from the start of one infusion to the start of the subsequent infusion.
dFor treatment of cIAI, administer metronidazole concurrently.

2.2 Recommended Dosage in Adults with Estimated Creatinine Clearance Less than or Equal to 50 mL/min

Table 2 shows the recommended dosage to be administered by intravenous (IV) infusion over 3 hours in adults with estimated creatinine clearance (CLcr) less than or equal to 50 mL/min. In patients with renal impairment, close monitoring of estimated CLcr is advised. In some patients, the CLcr estimated from serum creatinine can change quickly, especially early in the course of treatment for the infection. For treatment of cIAI, administer metronidazole concurrently.

Table 2. Recommended dosage for adults with estimated CLcr less than or equal to 50 mL/min
Estimated CLcr (mL/min) a | Recommended Dose for EMBLAVEO (aztreonam and avibactam) b,c |  | Dosing Intervald
Greater than 30 to less than or equal to 50 mL/min | Loading | EMBLAVEO 2.67 g (aztreonam 2 grams and avibactam 0.67 grams) | Every 6 hours
 | Maintenance | EMBLAVEO 1 g (aztreonam 0.75 grams and avibactam 0.25 grams)
Greater than 15 to less than or equal to 30 mL/min | Loading | EMBLAVEO 1.8 g (aztreonam 1.35 grams and avibactam 0.45 grams) | Every 8 hours
 | Maintenance | EMBLAVEO 0.9 g (aztreonam 0.675 grams and avibactam 0.225 grams)
Less than or equal to 15, including on hemodialysise | Loading | EMBLAVEO 1.33 g (aztreonam 1 gram and avibactam 0.33 grams) | Every 12 hours
 | Maintenance | EMBLAVEO 0.9 g (aztreonam 0.675 grams and avibactam 0.225 grams)
aCalculated using the Cockcroft-Gault formula
bAztreonam-avibactam is a combination product in a fixed 3:1 ratio. A single loading dose is followed by maintenance doses beginning at the next dosing interval.
cThe total duration of treatment is for 5 days to 14 days.
dDosing interval is calculated from the start of one infusion to the start of the subsequent infusion.
eBoth aztreonam and avibactam are hemodialyzable; thus, administer EMBLAVEO after hemodialysis on hemodialysis days.

2.3 Preparation of EMBLAVEO Solution for Administration

EMBLAVEO is supplied as a lyophilized powder, which must be reconstituted and subsequently diluted, using aseptic technique prior to intravenous infusion. Prepare the reconstituted and diluted solutions of EMBLAVEO using the steps described below.

Parenteral drug products should be inspected visually for particulate matter and discoloration prior to administration, whenever solution and container permit.

a) Reconstitute the powder in the EMBLAVEO vial with 10 mL of Sterile Water for Injection.

b) Mix the reconstituted vial gently and ensure that the contents are dissolved completely.

- The reconstituted EMBLAVEO solution is not for direct injection. The reconstituted solution must be diluted before intravenous infusion.
- The reconstituted EMBLAVEO solution will have an approximate aztreonam concentration of 127 mg/mL and an approximate avibactam concentration of 42.3 mg/mL. The final volume is approximately 12 mL.

c) Prepare the required dose for intravenous infusion by withdrawing the appropriate volume determined from Table 3 from the reconstituted vial. Discard unused portion.

Table 3. Preparation of EMBLAVEO Doses for Intravenous Infusion
Dose (EMBLAVEO) |  |  | Volume to withdraw from Constituted Vial for Further Dilution to 50 mL to 250 mL
 | Estimated CLcra (mL/min) | EMBLAVEO (g) (aztreonam (grams) and avibactam (grams))
Loading | Greater than 50 mL/min | EMBLAVEO 2.67 g (aztreonam 2 grams and avibactam 0.67 grams) | 15.7 mL (requires two vials; discard unused portions)
 | Greater than 30 mL/min to less than or equal to 50 mL/min | EMBLAVEO 2.67 g (aztreonam 2 grams and avibactam 0.67 grams) | 15.7 mL (requires two vials; discard unused portions)
 | Greater than 15 mL/min to less than or equal to 30 mL/min | EMBLAVEO 1.8 g (aztreonam 1.35 grams and avibactam 0.45 grams) | 10.6 mL
 | Less than or equal to 15 mL/min | EMBLAVEO 1.33 g (aztreonam 1 gram and avibactam 0.33 grams) | 7.9 mL
Maintenance | Greater than 50 mL/min | EMBLAVEO 2 g (aztreonam 1.5 grams and avibactam 0.5 grams) | Entire contents of one vial (approximately 12 mL)
 | Greater than 30 mL/min to less than or equal to 50 mL/min | EMBLAVEO 1 g (aztreonam 0.75 grams and avibactam 0.25 grams) | 5.9 mL
 | Greater than 15 mL/min to less than or equal to 30 mL/min | EMBLAVEO 0.9 g (aztreonam 0.675 grams and avibactam 0.225 grams) | 5.3 mL
 | Less than or equal to 15 mL/min | EMBLAVEO 0.9 g (aztreonam 0.675 grams and avibactam 0.225 grams) | 5.3 mL
aCalculated using the Cockcroft-Gault formula

d) Before infusion, dilute the withdrawn volume of the reconstituted EMBLAVEO solution further to 50 mL to 250 mL in an infusion bag containing any of the following: 0.9 % sodium chloride for injection or 5% dextrose solution for injection or lactated Ringer’s injection, to achieve an aztreonam concentration of 2.7 mg/mL to 40 mg/mL and an avibactam concentration of 0.9 mg/mL to 13.3 mg/mL.

e) Mix gently and ensure that the contents are dissolved completely. Visually inspect the diluted EMBLAVEO solution for particulate matter and discoloration prior to administration (the color of the EMBLAVEO infusion solution for administration ranges from clear, colorless to yellow).

2.4 Drug Compatibility

The EMBLAVEO solution for administration is compatible with Sterile Water for Injection, for reconstitution and any of the following diluents for further dilution of the reconstituted solution:

- 0.9% Sodium chloride injection
- 5% Dextrose injection
- Lactated Ringer's injection

The compatibility of EMBLAVEO with other medicinal products has not been established. EMBLAVEO should not be mixed with or physically added to solutions containing other medicinal products.

2.5 Storage of Reconstituted and Diluted EMBLAVEO Solutions

Reconstituted Solution

Upon reconstitution with Sterile Water for Injection, the reconstituted EMBLAVEO solution may be held for up to 60 minutes at 30°C (86°F) under ambient light prior to transfer and dilution in a suitable infusion bag.

Diluted Reconstituted Solution

Following dilution of the reconstituted solution with 0.9% sodium chloride injection or 5 % dextrose injection or lactated Ringer’s injection, EMBLAVEO solution in the infusion bags may be stored based on conditions outlined in Table 4.

Table 4. Storage of Diluted Solutions
Diluent used for Dilution following Reconstitution | Storage
0.9% Sodium Chloride Injection Or Lactated Ringer’s Injection | Refrigerate at 2°C to 8°C (36°F to 46°F) for up to 24 hours followed by 12 hours at not more than 30°C (86°F) under ambient light. Discard unused portion.
5% Dextrose Injection | Refrigerate at 2°C to 8°C (36°F to 46°F) for up to 24 hours followed by 4 hours at not more than 30°C (86°F) under ambient light. Discard unused portion.

3 DOSAGE FORMS AND STRENGTHS

EMBLAVEO (aztreonam and avibactam) for injection is supplied as a white to slightly yellow sterile lyophilized powder for reconstitution in a single-dose, sterile, clear glass vial containing:

2 g aztreonam and avibactam (1.5 grams aztreonam and 0.5 grams avibactam (equivalent to 0.542 grams of avibactam sodium)).

4 CONTRAINDICATIONS

EMBLAVEO is contraindicated in patients with known hypersensitivity to the components of EMBLAVEO (aztreonam and avibactam) [see Warnings and Precautions (5.1)].

5 WARNINGS AND PRECAUTIONS

5.1 Hypersensitivity Reactions

Hypersensitivity reactions were noted in patients treated with EMBLAVEO, including rash, flushing, and bronchospasm [see Adverse Reactions (6.1)].

Prior to treatment, it should be established if the patient has a history of hypersensitivity reactions to components of EMBLAVEO (aztreonam and avibactam). In case of hypersensitivity reactions, immediately discontinue EMBLAVEO and initiate appropriate medications and/or supportive care.

5.2 Serious Skin Disorders

Cases of toxic epidermal necrolysis have been reported in association with aztreonam (a component of EMBLAVEO) in patients undergoing bone marrow transplant with multiple risk factors including sepsis, radiation therapy, and other concomitantly administered drugs associated with toxic epidermal necrolysis. Discontinue EMBLAVEO if a serious skin reaction occurs.

5.3 Hepatic Adverse Reactions

Elevations in hepatic transaminases have been observed during treatment with EMBLAVEO [see Adverse Reactions (6.1)]. Monitoring of liver-related laboratory tests is recommended while on treatment, particularly in patients with baseline liver comorbidities or on concomitant hepatotoxic medications. If transaminase elevations are noted, consider discontinuing EMBLAVEO, if clinically indicated, and monitor the patient for resolution of any pertinent clinical and laboratory findings.

5.4 Clostridioides Difficile-Associated Diarrhea

Clostridioides difficile-associated diarrhea (CDAD) has been reported for nearly all systemic antibacterial drugs, including EMBLAVEO, and may range in severity from mild diarrhea to fatal colitis. Treatment with antibacterial drugs alters the normal flora of the colon and may permit overgrowth of C. difficile. C. difficile produces toxins A and B which contribute to the development of CDAD. Hypertoxin producing strains of C. difficile cause increased morbidity and mortality, as these infections can be refractory to antimicrobial therapy and may require colectomy. CDAD must be considered in all patients who present with diarrhea following antibacterial use. Careful medical history is necessary because CDAD has been reported to occur more than 2 months after the administration of antibacterial drugs. If CDAD is suspected or confirmed, antibacterial drugs not directed against C. difficile may need to be discontinued. Manage fluid and electrolyte levels as appropriate, supplement protein intake, monitor antibacterial treatment of C. difficile, and institute surgical evaluation as clinically indicated.

5.5 Development of Drug-Resistant Bacteria

Prescribing EMBLAVEO in the absence of a proven or strongly suspected bacterial infection is unlikely to provide benefit to the patient and increases the risk of the development of drug-resistant bacteria [see Indications and Usage (1.2)].

6 ADVERSE REACTIONS

The following adverse reactions are discussed in greater detail in the Warnings and Precautions section:

- Hypersensitivity Reactions [see Warnings and Precautions (5.1)]
- Serious Skin Disorders [see Warnings and Precautions (5.2)]
- Hepatic Adverse Reactions [see Warnings and Precautions (5.3)]
- Clostridioides Difficile-Associated Diarrhea [see Warnings and Precautions (5.4)]

6.1 Clinical Trials Experience

Because clinical trials are conducted under widely varying conditions, adverse reaction rates observed in the clinical trials of a drug cannot be directly compared to rates in the clinical trials of another drug and may not reflect the rates observed in practice.

Clinical Trials Experience in Adult Patients

Three clinical trials, Trial 1, Trial 2, and Trial 3, underly the EMBLAVEO clinical development program. Trial 1 was a randomized, comparative trial conducted in patients with cIAI and hospital-acquired bacterial pneumonia/ventilator-associated bacterial pneumonia (HABP/VABP) (not an approved indication for EMBLAVEO), while Trials 2 and 3 were smaller, noncomparative trials conducted in patients with cIAI as well as other serious infections caused by gram negative pathogens expressing metallo-beta-lactamases. The safety data from Trial 1 are summarized below.

In Trial 1, EMBLAVEO was evaluated in a comparative clinical trial in patients with cIAI or HABP/VABP; note that EMBLAVEO is not approved for the treatment of HABP/VABP. Trial 1 evaluated 275 patients treated with EMBLAVEO and 137 patients treated with comparator (meropenem +/- colistin); 203 EMBLAVEO-treated patients had a diagnosis of cIAI while 72 EMBLAVEO-treated patients had a diagnosis of HABP/VABP (not an approved indication for EMBLAVEO).

Patients received treatment with EMBLAVEO 2 grams (aztreonam 1.5 grams and avibactam 0.5 grams) or comparator for 5 to 14 days. Patients randomized to EMBLAVEO received a loading dose of aztreonam and avibactam administered by intravenous infusion over 30 minutes immediately followed by an extended loading dose infused over 3 hours, followed by maintenance doses infused over 3 hours every 6 hours based on the participant’s creatinine clearance. Patients with cIAI randomized to EMBLAVEO also received metronidazole 500 mg administered by intravenous infusion over 60 minutes every 8 hours.

The median age of patients in Trial 1 treated with EMBLAVEO was 58 years, ranging between 18 and 87 years old. Patients treated with EMBLAVEO were predominantly male (66%) and White (59%). Approximately 40% (22% of cIAI and 89% of HABP/VABP; not an approved indication) of patients treated with EMBLAVEO had an APACHE II score greater than 10 at baseline.

Death occurred in 6.9% (19/275) of patients who received EMBLAVEO and in 8% (11/137) of patients who received comparator. In patients with cIAI, death occurred in 3.0% (6/203) of patients treated with EMBLAVEO and 2.9% (3/103) in patients treated with comparator. Overall, 3.6% (10/275) of the patients who received EMBLAVEO discontinued treatment due to an adverse reaction, compared with 3.6% (5/137) of patients treated with comparator.

Common adverse reactions occurring in greater than 5% of patients are noted in the table below.

Table 5: Adverse Reactions Occurring in > 5% of Patients in the EMBLAVEO Treatment Arm in Trial 1
Adverse Reactions | EMBLAVEO ± Metronidazole (N=275) n (%) | Meropenem ± Colistin (N=137) n (%)
Hepatic adverse reactions* | 40 (14.5) | 16 (11.7)
Anemia** | 22 (8.0) | 7 (5.1)
Diarrhea | 16 (5.8) | 5 (3.6)
Hypokalemia | 16 (5.8) | 4 (2.9)
Pyrexia*** | 16 (5.8) | 7 (5.1)
*Includes AR terms alanine aminotransferase increased, aspartate aminotransferase increased, hepatic function abnormal, hypertransaminasemia, transaminases increased, hepatic enzyme increased, liver injury
**Includes anemia, hemoglobin decreased
***Includes pyrexia, hyperpyrexia, hyperthermia, body temperature increased

Hepatic Adverse Reactions

In Trial 1, 40/275 patients (15%) in the EMBLAVEO arm had hepatic adverse reactions compared to 16/137 (12%) in the comparator arm receiving meropenem with or without colistin. In Trial 1, 10 (3.8%) patients in the EMBLAVEO arm compared to 4 (3.1%) patients in the comparator arm had an ALT elevation greater than or equal to 5 x ULN. No Hy’s Law cases in the EMBLAVEO or comparator arm were seen in Trials 1, 2, and 3. EMBLAVEO was discontinued due to hepatic enzyme elevations in 4 patients in Trials 1, 2, and 3. The transaminase elevations resolved when EMBLAVEO was discontinued.

The following adverse reactions were reported in EMBLAVEO-treated patients at a rate of less than 5% in Trial 1:

- Vascular disorders: Phlebitis, flushing, hypotension
- Skin and subcutaneous tissue disorders: Rash (includes rash and rash macular), dermatitis (includes dermatitis allergic, dermatitis), erythema
- Gastrointestinal Disorders: Vomiting, nausea, abdominal pain (includes abdominal pain, abdominal pain upper, abdominal pain lower), constipation
- Nervous System Disorders: Mental status change (includes mental status changes, delirium, confusional state, and disorientation), dizziness, headache, sleep disorder (includes sleep disorder, insomnia), ageusia, asthenia
- Infectious Diseases: Clostridioides difficile infection (includes Clostridioides difficile infection and Clostridioides difficile colitis)
- Hematologic: Coagulopathy, leukocytosis (includes white blood cell count increased and leukocytosis), thrombocytopenia (includes thrombocytopenia, platelet count decreased); thrombocytosis (includes thrombocytosis, platelet count increased), eosinophilia
- Hypersensitivity: Bronchospasm

Additionally, adverse reactions that have been reported with aztreonam alone that were not reported in EMBLAVEO-treated patients in Trial 1 are listed below:

Hypersensitivity: Anaphylaxis, angioedema

Hematologic: Pancytopenia, neutropenia

Dermatologic: Purpura, erythema multiforme, exfoliative dermatitis, urticaria, petechiae, pruritus, diaphoresis

Cardiovascular: Transient ECG changes (ventricular bigeminy and PVC)

Respiratory: Wheezing, dyspnea, chest pain

Hepatobiliary: Hepatitis, jaundice

Nervous System: Seizure, encephalopathy, vertigo, paresthesia

Musculoskeletal: Muscular aches

Special Senses: Tinnitus, diplopia, numb tongue, sneezing, nasal congestion, halitosis

Other: Vaginal candidiasis, vaginitis, breast tenderness

Body as a Whole: Malaise

Adverse Laboratory Changes reported with aztreonam alone that were not reported in EMBLAVEO-treated patients in Trial 1 are listed below:

Hematologic: Positive Coombs’ test

Renal: Increases in serum creatinine

Trial 2 was a noncomparative study of EMBLAVEO in 34 subjects with cIAI. Trial 3 was a comparative study of EMBLAVEO versus best available therapy in patients with serious infections due to multi-drug resistant gram-negative bacteria producing metallo-beta-lactamases (not an approved indication for EMBLAVEO); 12 patients were treated in the EMBLAVEO arm and 2 patients were treated in the comparator arm. The safety findings for the EMBLAVEO treatment arm in Trials 2 and 3 were similar to those of Trial 1.

7 DRUG INTERACTIONS

7.1 OAT 1 and 3 Transport Inhibitors

Concomitant use of organic anion transporter (OAT) 1 and OAT 3 transporter inhibitors (e.g., probenecid) with EMBLAVEO is not recommended. There is insufficient information to characterize the effect of concomitant use of OAT 1/3 transport inhibitors with EMBLAVEO [see Clinical Pharmacology (12.3)].

8 USE IN SPECIFIC POPULATIONS

8.1 Pregnancy

Risk Summary

There are no data on the effects of EMBLAVEO use in pregnant women to evaluate for a drug-associated risk of major birth defects, miscarriage or other adverse maternal or fetal outcomes. Available data from case reports over several decades with aztreonam and over approximately a decade with avibactam have not identified a drug-associated risk of major birth defects, miscarriage or other maternal or fetal outcomes.

Aztreonam

Developmental toxicity studies in pregnant rats and rabbits with daily doses of aztreonam revealed no evidence of embryotoxicity, fetotoxicity, or fetal malformations at doses 2.7- and 3.6-fold greater, respectively, than the maximum recommended human dose (MRHD) for adults of 6.5 g per day. In a peri/postnatal development (PPND) study in rats, no aztreonam-induced changes in any maternal, fetal, or neonatal parameters were observed at a dose 2.7-fold greater than the MRHD.

Avibactam

Avibactam administered to pregnant rats was not associated with fetal malformations at doses 6 times the MRHD of 2.17 g per day. In pregnant rabbits, avibactam administered in doses greater than or equal to 5 times the MRHD was associated with increased post-implantation loss, lower mean fetal weights, delayed ossification of several bones and other anomalies. In a rat PPND study, there were no effects on pup growth and viability at doses up to 8 times the avibactam MRHD. A dose-related increase in the incidence of renal pelvic and ureter dilatation was observed in female weaning pups with renal pelvic dilatation persisting into adulthood (see Data).

The background risk of major birth defects and miscarriage for the indicated population is unknown. All pregnancies have a background risk of birth defect, loss or other adverse outcomes. In the US general population, the estimated background risk of major birth defects and miscarriage in clinically recognized pregnancies is 2% to 4% and 15% to 20%, respectively.

Data

Animal Data

Aztreonam

Developmental toxicity studies in pregnant rats and rabbits with daily doses of aztreonam up to 1800 and 1200 mg/kg, respectively, revealed no evidence of embryotoxicity or fetotoxicity or fetal malformations. These doses, based on body surface area, are 2.7- and 3.6-fold greater than the MRHD for adults of 6.5 g per day.

A peri/postnatal study in rats revealed no drug-induced changes in any maternal, fetal, or neonatal parameters. The highest dose used in this study, 1800 mg/kg/day, is 2.7 times the MRHD based on body surface area comparison.

Avibactam

Avibactam did not produce fetal malformations in pregnant rats or rabbits. In the rat, intravenous studies with 0, 250, 500 and 1000 mg/kg/day of avibactam during gestation days 6-17 showed no embryo-fetal toxicity at doses up to 1000 mg/kg/day, approximately 6 times the MRHD (2.17 g/day) based on exposure (AUC).

Pregnant rabbits administered intravenous avibactam on gestation days 6-19 at 0, 100, 300 and 1000 mg/kg/day showed no effects on embryo-fetal development at a dose of 100 mg/kg, twice the MRHD based on AUC comparison. At doses greater than or equal to 300 mg/kg/day (5 times the MRHD based on AUC comparison), increased post-implantation loss, lower mean fetal weights, delayed ossification of several bones and other anomalies were observed.

In a rat pre-and post-natal study at up to 825 mg/kg/day intravenously (8 times the MRHD based on AUC), there were no effects on pup growth and viability. A dose-related increase in the incidence of renal pelvic and ureter dilatation was observed in female weaning pups that was not associated with pathological changes to renal parenchyma or renal function, with renal pelvic dilatation persisting after female weaning pups became adults.

8.2 Lactation

Risk Summary

Aztreonam is present in human milk at concentrations that are less than 1% of those determined in simultaneously obtained maternal serum. There are no data on the presence of avibactam in human milk. Avibactam is present in the milk of rats (see Data). When a drug is present in animal milk, it is likely that the drug will be present in human milk. There are no data on the effects of aztreonam or avibactam on the breastfed infant or the effects on milk production.

The developmental and health benefits of breastfeeding should be considered along with the mother's clinical need for EMBLAVEO and any potential adverse effects on the breast-fed infant from EMBLAVEO or from the underlying maternal condition.

Data

In a rat pre- and post-natal study at doses up to 825 mg/kg/day intravenously (8 times the human exposure based on AUC), the exposure to avibactam was minimal in the pups in comparison to the dams. Exposure to avibactam was observed in both pups and milk on PND 7.

8.4 Pediatric Use

The safety and effectiveness of EMBLAVEO in pediatric patients less than 18 years of age have not been established.

8.5 Geriatric Use

In Trials 1, 2, and 3, there were 103 patients in the EMBLAVEO treatment arm 65 years of age and older. Of these patients, 60 (58%) were between 65-74 years of age and 43 (42%) patients were 75 years of age and older. In comparison, there were 202 patients in the EMBLAVEO treatment arm less than 65 years of age. Clinical studies of EMBLAVEO did not include sufficient numbers of patients aged 65 years and over to determine whether they respond differently from younger patients. Other reported clinical experience has not identified differences in responses between the elderly and younger patients.

Aztreonam and avibactam (components of EMBLAVEO) are known to be substantially excreted by the kidney, and the risk of adverse reactions to aztreonam and avibactam (components of EMBLAVEO) may be greater in patients with impaired renal function. Because elderly patients are more likely to have decreased renal function, care should be taken in dose selection, and it may be useful to monitor renal function. No dosage adjustment is required in elderly patients based on age; the dose should be selected based on renal function [see Dosage and Administration (2.2) and Clinical Pharmacology (12.3)].

8.6 Renal Impairment

Aztreonam and avibactam, the components of EMBLAVEO, are primarily renally excreted. Plasma exposures of both aztreonam and avibactam increase with decreasing renal function, therefore dosage adjustments are recommended for EMBLAVEO to compensate for the slower rate of renal clearance in patients with CLcr less than 50 mL/min [see Dosage and Administration (2.2) and Clinical Pharmacology (12.3)].

Monitor creatinine clearance in patients with changing renal function and adjust the dose of EMBLAVEO accordingly. Both aztreonam and avibactam are hemodialyzable; thus, EMBLAVEO should be administered after hemodialysis on hemodialysis days [see Dosage and Administration (2.2) and Clinical Pharmacology (12.3)].

10 OVERDOSAGE

There is no information on the clinical signs and symptoms associated with an overdose of EMBLAVEO. Aztreonam and avibactam can be partially removed by hemodialysis [see Clinical Pharmacology (12.3)]. No clinical information is available on the use of hemodialysis to treat EMBLAVEO overdosage.

11 DESCRIPTION

EMBLAVEO for injection, for intravenous use, is a combination product consisting of aztreonam and avibactam sodium.

Aztreonam

Aztreonam is a synthetic, monobactam antibacterial drug. Its chemical name is (Z)-2-[[[(2-Amino-4-thiazolyl)[[(2S,3S)-2-methyl-4-oxo-1-sulfo-3-azetidinyl]carbamoyl]methylene]amino]oxy]-2-methylpropionic acid. Its molecular weight is 435.43 g/mol. The empirical formula is C13H17N5O8S2.

Figure 1. Chemical structure of aztreonam

Avibactam

Avibactam sodium is a beta-lactamase inhibitor. Its chemical name is sodium [(2S,5R)-2-carbamoyl-7-oxo-1,6- diazabicyclo[3.2.1]octan-6-yl] sulfate. Its molecular weight is 287.23 g/mol. The empirical formula is C7H10N3O6SNa.

Figure 2. Chemical structure of avibactam sodium

EMBLAVEO 2 grams (aztreonam 1.5 grams and avibactam 0.5 grams) for injection is a white to slightly yellow sterile powder for reconstitution consisting of aztreonam and avibactam packaged in glass vials. The formulation also contains inactive ingredient L-arginine 1170 mg/vial.

Each EMBLAVEO 2 grams single-dose vial contains 1.5 grams aztreonam and 0.5 grams avibactam (equivalent to 0.542 gram sterile avibactam sodium). The total sodium content of the mixture is approximately 44.6 mg/vial.

12 CLINICAL PHARMACOLOGY

12.1 Mechanism of Action

EMBLAVEO is an antibacterial drug [see Microbiology (12.4)].

12.2 Pharmacodynamics

As with other beta-lactam antimicrobial drugs, the time that unbound plasma concentrations of aztreonam exceed the EMBLAVEO minimum inhibitory concentration (MIC) against the infecting organism has been shown to best correlate with efficacy in a neutropenic murine thigh infection model with Enterobacterales. The time above a threshold concentration has been determined to be the parameter that best predicts the efficacy of avibactam in combination with aztreonam in in vitro and in vivo nonclinical models.

Cardiac Electrophysiology

Avibactam does not prolong the QTc interval to any clinically significant extent at a dose 3 times the maximum approved EMBLAVEO recommended avibactam loading dose.

Aztreonam QT prolongation evaluations have not been conducted or reported in literature.

12.3 Pharmacokinetics

Following single or multiple dosing, the Cmax and AUC of both aztreonam and avibactam (components of EMBLAVEO) increase in an approximate dose-proportional manner over a dose range of 500 mg to 2000 mg aztreonam (0.25 to 1 times the approved maximum recommended loading dose) and of 50 mg to 2000 mg avibactam (0.07 to 3 times the approved maximum recommended loading dose).

Aztreonam and avibactam (components of EMBLAVEO) pharmacokinetic properties are summarized in Table 6. There is minimal accumulation of aztreonam and avibactam following multiple intravenous 3-hour infusions of EMBLAVEO every 6 hours in patients with normal renal function.

Table 6: Pharmacokinetic (PK) Properties of Components of EMBLAVEO (Aztreonam and Avibactam)
PK Parameter | Aztreonam | Avibactam
Cmax, ss (mg/L)a,b, c | 54.46 ± 17.22 | 11.29 ± 3.89
AUC0-24, ss (mg•h/L)a,b,c | 841.22 ± 317.59 | 165.7 ± 65.63
Distribution
Binding to human plasma proteins | 38 % | 8 %
Volume of distribution (Vss)c | 21.4 ± 23 L | 37.8 ± 73 L
Elimination
Clearance (CL)c | 10.2 ± 22 L/hr | 18 ± 39 L/hr
Mean terminal half-life (t1/2)c | 2.03 ± 0.69 hrs | 2.04 ± 0.52 hrs
Metabolism
Metabolic pathways | Aztreonam is minimally metabolized. No metabolism of avibactam was observed in human liver preparations (microsomes and hepatocytes). Unchanged avibactam was the major drug-related component in human plasma and urine following dosing with [^14C]-avibactam
Excretion
Major route of elimination | Renal excretion: tubular secretion and glomerular filtration
% of dose excreted in urine, unchanged | 64.2 % to 75.9 % | 83.8 % to 100 %
% of dose excreted in feces, changed and unchanged | Approximately 12 % | < 0.25 %
Cmax, ss =maximum plasma concentration at steady-state; AUC0-24, ss=area under the plasma concentration-time curve from time zero up to 24 hrs at steady state; Vss = volume of distribution at steady state; mean = arithmetic mean; SD = standard deviation.
a2000 mg aztreonam + 670 mg avibactam IV infusion over 3 hours then 1500 mg aztreonam + 500 mg avibactam IV infusion over 3 hours every 6 hours.
bThere is no clinically significant PK differences (as measured by AUC and Cmax) between healthy adults and adults with cIAI (normal renal function).
cmean ± SD reported based on PK data from 97 adults with cIAI

Specific Populations

No clinically significant differences in the pharmacokinetics of aztreonam or avibactam were observed based on age (range: 18-89 years), sex (62.1% male), race (61.9% White, 27.7% Asian, and 3.4% Black), or BMI (10.4 to 62.5 kg/m^2).

Patients with Renal Impairment

The disposition of aztreonam and avibactam were evaluated in non-infected subjects with CLcr >80 mL/min (as measured by Cockcroft-Gault method, n=6) administered the recommended general maintenance dosing regimen and with CLcr 32 to 37 mL/min (n=5) administered the recommended adjusted maintenance dosing regimen for CLcr >15 to ≤ 30 mL/min. Aztreonam AUC24 and Cmax at steady state is approximately 21% and 24% lower in the subjects with CLcr 32 to 37 mL/min compared to the CLcr >80 mL/min group. The avibactam AUC24 and Cmax at steady state are approximately 24% and 2% higher in the subjects with CLcr 32 to 37 mL/min, compared to the CLcr >80 mL/min group. Dosage adjustment for EMBLAVEO in patients with CLcr ≤ 50 mL/min is recommended [see Dosage and Administration (2.2)].

Patients with Hepatic Impairment

EMBLAVEO has not been studied in patients with hepatic impairment. As aztreonam and avibactam do not appear to undergo significant hepatic metabolism, the systemic clearance of either active substance is not expected to be significantly altered by hepatic impairment.

Dosage adjustments are not considered necessary for EMBLAVEO in patients with impaired hepatic function.

Geriatric Patients (Greater than or equal to 65 years)

Mean elimination half-life of both aztreonam and avibactam is increased, and plasma clearance decreased in the elderly, consistent with age-related reduction in renal clearance of aztreonam and avibactam.

Dosage adjustment for EMBLAVEO in geriatric patients should be based on renal function [see Dosage and Administration (2.2)].

Drug Interaction Studies

Clinical Studies and Model-Informed Approaches

OAT1/3 inhibitors: No clinically significant differences in aztreonam pharmacokinetics were observed when used concomitantly with probenecid (OAT1/3 inhibitors). Concomitant administration of probenecid with aztreonam is reported to result in clinically insignificant increases in aztreonam exposure. No clinical studies have been conducted with avibactam and OAT1/3 inhibitors (e.g., probenecid) and the clinical impact of OAT inhibitors on the pharmacokinetics of avibactam is not known.

Other: No drug-drug interaction was observed between aztreonam, avibactam, and metronidazole in clinical studies.

In Vitro Studies

Avibactam was not found to be an inhibitor of the following hepatic and renal transporters in vitro at clinically relevant concentrations: MDR1, BCRP, OAT1, OAT3, OATP1B1, OATP1B3, BSEP, MRP4, OCT1, or OCT2. Avibactam was not a substrate of MDR1, BCRP, MRP4, or OCT2, but was a substrate of human OAT1 and OAT3 kidney transporters based on results generated in human embryonic kidney cells expressing these transporters.

12.4 Microbiology

Mechanism of action

EMBLAVEO is a combination of the monobactam antibacterial, aztreonam, and the beta-lactamase inhibitor, avibactam. Aztreonam inhibits bacterial peptidoglycan cell wall synthesis following binding to penicillin binding proteins (PBPs), which leads to bacterial cell lysis and death and is stable to class B beta-lactamase enzymes (metallo-beta-lactamases). Avibactam is a non-beta-lactam, beta-lactamase inhibitor that acts by forming a covalent adduct with the enzyme that is stable to hydrolysis. Avibactam inhibits both Ambler class A, class C and some class D beta-lactamases, including extended-spectrum β-lactamases (ESBLs), Klebsiella pneumoniae carbapenemase (KPC), OXA-48 carbapenemases, and AmpC enzymes. Avibactam does not inhibit class B enzymes and is not able to inhibit some class D enzymes.

EMBLAVEO demonstrated in vitro activity against Enterobacterales isolates expressing beta-lactamases included in Ambler Class A (CTX-M-, TEM-, and SHV-type ESBLs; KPC carbapenemase), Class B (New Delhi metallo-beta-lactamases [NDM], Verona integron-encoded metallo-beta-lactamase [VIM], and imipenemases [IMP]), Class C (AmpC), and Class D (OXA-48-like).

Resistance

Resistance mechanisms to EMBLAVEO include beta-lactamase enzymes refractory to inhibition by avibactam and able to hydrolyze aztreonam, mutant or acquired PBPs, decreased outer membrane permeability, and active efflux pumps.

Interaction with Other Antimicrobials

No antagonism was demonstrated in in vitro studies between EMBLAVEO and amikacin, ciprofloxacin, colistin, daptomycin, gentamicin, levofloxacin, linezolid, metronidazole, tigecycline, tobramycin, and vancomycin against Enterobacterales.

Activity against bacteria in animal infection models

Avibactam restored the activity of aztreonam in animal models of infection (e.g., mouse thigh infection, mouse lung infection) caused by aztreonam non-susceptible NDM- and ESBL-producing E. coli and K. pneumoniae isolates. However, the clinical significance of these findings is unknown.

Antimicrobial Activity

EMBLAVEO has been shown to be active against most isolates of the following microorganisms both in vitro and in clinical infections [see Indications and Usage (1.1)].

- Citrobacter freundii complex
- Escherichia coli
- Enterobacter cloacae complex
- Klebsiella pneumoniae
- Klebsiella oxytoca
- Serratia marcescens

The following in vitro data are available, but their clinical significance is unknown. At least 90 percent of the following bacteria exhibit an in vitro MIC less than or equal to the susceptible breakpoint for EMBLAVEO against isolates of similar genus or organism group. However, the safety and effectiveness of EMBLAVEO in treating clinical infections due to these bacteria have not been established in adequate and well-controlled clinical trials:

Aerobic Gram-negative organisms

- Citrobacter koseri
- Enterobacter spp.
- Klebsiella aerogenes
- Morganella morganii
- Proteus mirabilis
- Proteus vulgaris
- Providencia rettgeri
- Providencia stuartii
- Raoultella ornithinolytica
- Serratia spp.
- Stenotrophomonas maltophilia

Susceptibility Test Methods

For specific information regarding susceptibility testing methods, interpretive criteria, and associated test methods and quality control standards recognized by FDA for EMBLAVEO, please see: https://www.fda.gov/STIC.

13 NONCLINICAL TOXICOLOGY

13.1 Carcinogenesis, Mutagenesis, Impairment of Fertility

Carcinogenesis

Aztreonam

Carcinogenicity studies with aztreonam have not been conducted using an intravenous route of administration. A 104-week rat inhalation toxicology study to assess the carcinogenic potential of aztreonam demonstrated no drug-related increase in the incidence of tumors. Rats were exposed to aerosolized aztreonam for up to 4 hours per day. Peak plasma levels of aztreonam averaging approximately 6.8 mcg/mL were measured in rats at the highest dose level.

Avibactam

Carcinogenicity studies with avibactam have not been conducted.

Mutagenesis

Aztreonam

Genetic toxicology studies performed with aztreonam in vitro (Ames test, mouse lymphoma forward mutation assay, gene conversion assay, chromosome aberration assay in human lymphocytes) and in vivo (mouse bone marrow cytogenetic assay) did not reveal evidence of mutagenic or clastogenic potential.

Avibactam

Avibactam was negative for genotoxicity in the Ames assay, unscheduled DNA synthesis, chromosomal aberration assay, and a rat micronucleus study.

Impairment of Fertility

Aztreonam

A two-generation reproduction study in rats at daily doses of 150, 600, or 2400 mg/kg/day given prior to and during gestation and lactation, revealed no evidence of impaired fertility. Based on body surface area, the high dose is 3.6-fold greater than the maximum recommended human dose (MRHD) for adults of 6.5 g per day. There was a slightly reduced survival rate during the lactation period in the offspring of rats that received the highest dose, but not in offspring of rats that received lower doses of aztreonam.

Avibactam

Avibactam had no adverse effects on fertility of male and female rats given up to 1g/kg/day (approximately 4.5-fold higher than the MRHD of 2.17 g/day on a body surface area basis). There was a dose-related increase in the percentage of pre-and post-implantation loss relative to controls, resulting in a lower mean litter size at doses of 0.5 g/kg/day (approximately 2 times the MRHD on a body surface area basis) and greater with intravenous administration to female rats beginning 2 weeks prior to mating.

14 CLINICAL STUDIES

14.1 Complicated Intra-abdominal Infections

The determination of efficacy of EMBLAVEO was supported in part by the previous findings of the efficacy and safety of aztreonam for the treatment of cIAI. The contribution of avibactam to EMBLAVEO was primarily established in vitro and in animal models of infection [see Clinical Pharmacology (12.4)]. EMBLAVEO was studied in one randomized, active-controlled, multicenter trial (Trial 1, NCT03329092) in patients with cIAI or hospital-acquired bacterial pneumonia/ventilator-associated bacterial pneumonia (HABP/VABP) (not an approved indication for EMBLAVEO). The trial was not designed with any formal hypotheses for inferential testing against the active comparator.

16 HOW SUPPLIED/STORAGE AND HANDLING

EMBLAVEO 2 grams (aztreonam and avibactam) for injection is supplied as a sterile powder in single-dose, clear glass vial containing: 1.5 grams aztreonam and 0.5 grams avibactam (equivalent to 0.542 grams of avibactam sodium).

Vials (NDC# 0074-3878-01) are supplied in cartons containing 10 vials.

EMBLAVEO vials should be stored at 2°C to 8°C (36°F to 46°F). Protect from light. Store in carton until time of use.

17 PATIENT COUNSELING INFORMATION

Serious Allergic Reactions

Advise patients, their families, or caregivers that allergic reactions, including serious allergic reactions, could occur that require immediate treatment. Ask them about any previous hypersensitivity reactions to EMBLAVEO, other beta-lactams, or other allergens [see Warnings and Precautions (5.1)].

Serious Skin Reactions

Advise patients about the signs and symptoms of serious skin manifestations such as sudden onset of a severe rash or blistering or peeling skin, possibly accompanied by a high fever or joint pain (these may be signs of more serious medical conditions such as toxic epidermal necrolysis) [see Warnings and Precautions (5.2)].

Potentially Serious Diarrhea

Advise patients, their families, or caregivers that diarrhea is a common problem caused by antibacterial drugs. Sometimes, frequent watery or bloody diarrhea may occur and may be a sign of a more serious intestinal infection. If severe watery or bloody diarrhea develops, tell them to contact his or her healthcare provider [see Warnings and Precautions (5.4)].

Antibacterial Resistance

Patients should be counseled that antibacterial drugs including EMBLAVEO should only be used to treat bacterial infections. They do not treat viral infections (e.g., the common cold). When EMBLAVEO is prescribed to treat a bacterial infection, patients should be told that although it is common to feel better early in the course of therapy, the medication should be taken exactly as directed. Skipping doses or not completing the full course of therapy may (1) decrease the effectiveness of the immediate treatment and (2) increase the likelihood that bacteria will develop resistance and will not be treatable by EMBLAVEO or other antibacterial drugs in the future [see Warnings and Precautions (5.5)].

Distributed by:
AbbVie Inc.
North Chicago, IL 60064

EMBLAVEO and its design are trademarks of Allergan Pharmaceuticals International Limited, an AbbVie company.

© 2025 AbbVie. All rights reserved.

PAA232843

Principal Display Panel

NDC 0074-3878-10

Rx Only

10 single-dose vials

Emblaveo™ 2g per vial*

(aztreonam and avibactam) for injection

*Aztreonam 1.5 grams and avibactam 0.5 grams (equivalent to 0.542 grams of avibactam sodium).

Single-Dose Vial. Discard Unused Portion

MUST BE RECONSTITUTED THEN DILUTED. FOR INTRAVENOUS INFUSION.